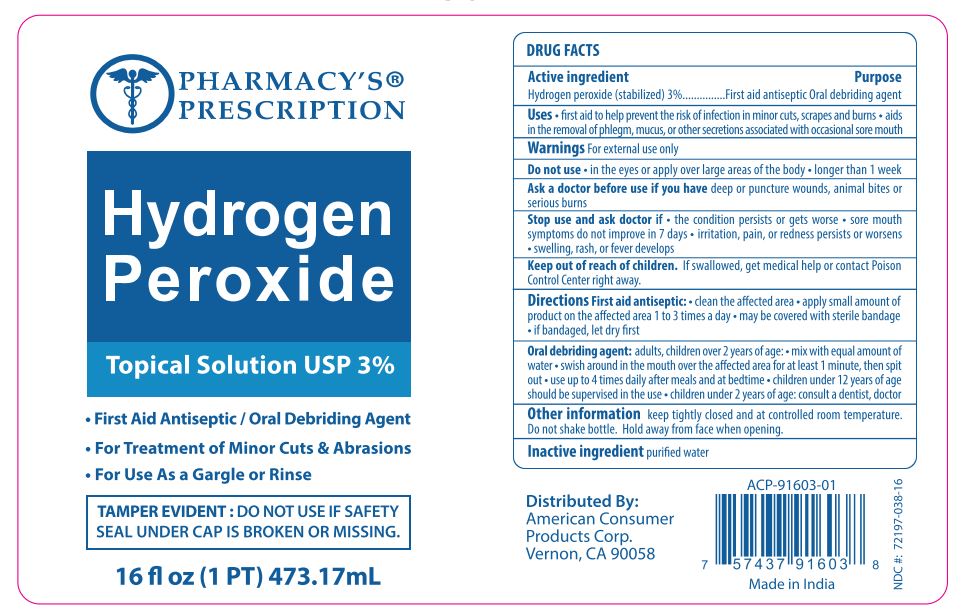 DRUG LABEL: Pharmacys Prescription Hydrogen Peroxide
NDC: 72197-038 | Form: LIQUID
Manufacturer: American Consumer Products Corp
Category: otc | Type: HUMAN OTC DRUG LABEL
Date: 20200914

ACTIVE INGREDIENTS: HYDROGEN PEROXIDE 3 mL/100 mL
INACTIVE INGREDIENTS: WATER

Pharmacys Prescription Hydrogen Peroxide 3%

Active Ingredient

Hydrogen peroxide (stabilized) 3%

Purpose

First aid antiseptic. Oral debriding agent.

Uses

Uses - first aid to help prevent the risk of infection in minor cuts, scrapes and burns. Aids in the removal of phlegm, mucus, or other secretions associated with occasional sore mouth.

Warnings

Warnings For external use only.

Do not use in the eyes, or apply over large ares of the body longer than 1 week.

Ask a doctor before use if you have deep puncture wounds, animal bites or serious burns.

Stop use

Stop use and ask doctor if • the condition persists or gets worse • sore mouth symptoms do not improve in 7 days • irritation, pain, or redness persists or worsens • swelling, rash, or fever develops.

Keep out of reach of children. If swallowed, get medical help or contact Poison Control Center right away.

Directions

First aid antiseptic: • clean the affected area • apply small amount of product on the affected area 1 to 3 times a day • may be covered with sterile bandage • if bandaged, let dry first.

Oral debriding agent: adults, children over 2 years of age: • mix with equal amount of water • swish around in the mouth over the affected area for at least 1 minute, then spit out • use up to 4 times daily after meals and at bedtime • children under 12 years of age should be supervised in the use children under 2 years of age: consult a dentist, doctor

Other information

Other information keep tightly closed and at controlled room temperature. Do not shake bottle. Hold away from face when opening.

Inactive ingredient

Inactive ingredient: purified water.

Distributed by

American Consumer Products Corp.

Vernon, CA 90058